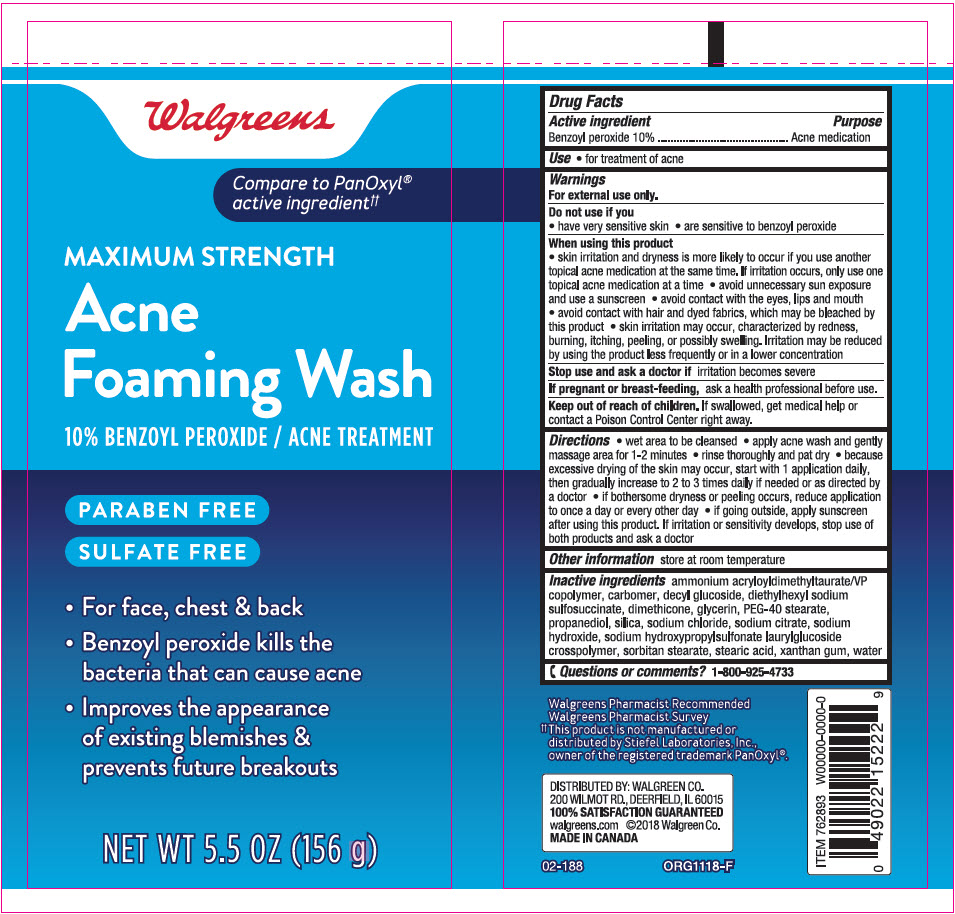 DRUG LABEL: Walgreens Acne Foaming Wash
NDC: 0363-1522 | Form: LOTION
Manufacturer: Walgreen Company
Category: otc | Type: HUMAN OTC DRUG LABEL
Date: 20241031

ACTIVE INGREDIENTS: Benzoyl Peroxide 100 mg/1 g
INACTIVE INGREDIENTS: AMMONIUM ACRYLOYLDIMETHYLTAURATE/VP COPOLYMER; CARBOMER HOMOPOLYMER, UNSPECIFIED TYPE; Decyl Glucoside; DOCUSATE SODIUM; Dimethicone; Glycerin; PEG-40 Stearate; Propanediol; SILICON DIOXIDE; Sodium Chloride; SODIUM CITRATE, UNSPECIFIED FORM; Sodium Hydroxide; SODIUM DECYLGLUCOSIDES HYDROXYPROPYLSULFONATE; SORBITAN MONOSTEARATE; Stearic Acid; Xanthan Gum; Water

Walgreens Acne Foaming Wash
Acne Medication

Drug Facts

Active ingredient

Benzoyl Peroxide 10%

Purpose

Acne medication

Use

- for treatment of acne

Warnings

For external use only.

Do not use if you

- have very sensitive
- are sensitive to benzoyl peroxide

When using this product

- skin irritation and dryness are more likely to occur if you use another topical acne medication at the same time. If irritation occurs, use only one topical acne medication at a time
- avoid unnecessary sun exposure and use a sunscreen
- avoid contact with the eyes, lips and mouth
- avoid contact with hair and dyed fabrics, which may be bleached by this product
- skin irritation may occur, characterized by redness, burning, itching, peeling, or possibly swelling. Irritation may be reduced by using the product less frequently or in a lower concentration.

Stop use and ask a doctor if irritation becomes severe

PREGNANCY OR BREAST FEEDING

If pregnant or breast-feeding, ask a health professional before use.

Keep out of reach of children. If swallowed, get medical help or contact a Poison Control Center right away.

Directions

- wet area to be cleansed
- apply acne wash and gently massage area for 1-2 minutes
- rinse thoroughly and pat dry
- because excessive drying of the skin may occur, start with 1 application daily, then gradually increase to 2 to 3 times daily if needed or as directed by a doctor
- if bothersome dryness or peeling occurs, reduce application to once a day or every other day
- if going outside, apply sunscreen after using this product. If irritation or sensitivity develops, stop use of both products and ask a doctor

Other information

Store at room temperature

Inactive ingredients

ammonium acryloyldimethyltaurate/VP copolymer, carbomer, decyl glucoside, diethylhexyl sodium sulfosuccinate, dimethicone, glycerin, PEG-40 stearate, propanediol, silica, sodium chloride, sodium citrate, sodium hydroxide, sodium hydroxypropylsulfonate laurylglucoside crosspolymer, sorbitan stearate, stearic acid, xanthan gum, water

Questions or comments?

1-800-925-4733

DISTRIBUTED BY: WALGREEN CO.
200 WILMONT RD., DEERFIELD, IL 60015

PRINCIPAL DISPLAY PANEL - 156 g Tube Label

Walgreens

Compare to PanOxyl®
active ingredient††

MAXIMUM STRENGTH

Acne
Foaming Wash

10% BENZOYL PEROXIDE / ACNE TREATMENT

PARABEN FREE
SULFATE FREE

- For face, chest & back
- Benzoyl peroxide kills the
  bacteria that can cause acne
- Improves the appearance
  of existing blemishes &
  prevents future breakouts

NET WT 5.5 OZ (156 g)